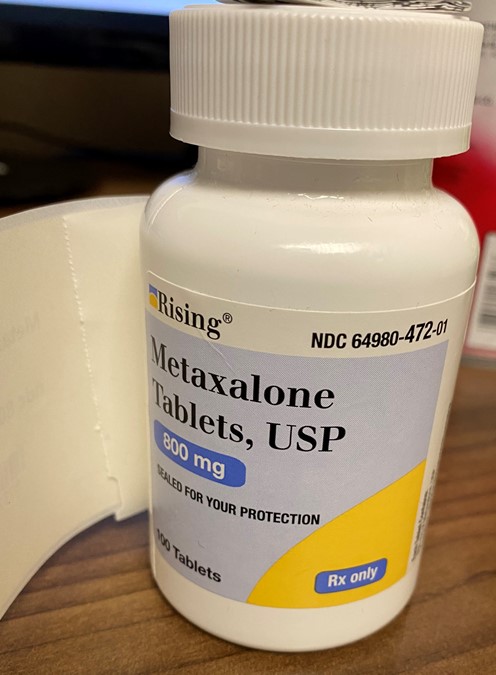 DRUG LABEL: Metaxalone
NDC: 80175-0472 | Form: TABLET
Manufacturer: Central Packaging
Category: prescription | Type: HUMAN PRESCRIPTION DRUG LABEL
Date: 20210225

ACTIVE INGREDIENTS: METAXALONE 800 mg/1 1

INDICATIONS AND USAGE

Metaxalone tablets are indicated as an adjunct to rest, physical therapy, and other measures for the relief of discomforts associated with acute, painful musculoskeletal conditions. The mode of action of this drug has not been clearly identified, but may be related to its sedative properties. Metaxalone does not directly relax tense skeletal muscles in man.